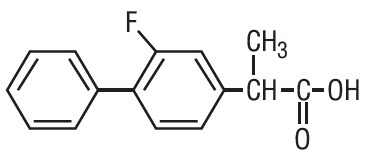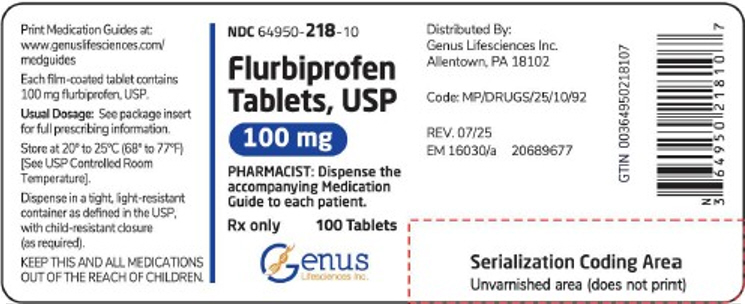 DRUG LABEL: Flurbiprofen
NDC: 64950-218 | Form: TABLET
Manufacturer: Genus Lifesciences
Category: prescription | Type: HUMAN PRESCRIPTION DRUG LABEL
Date: 20260203

ACTIVE INGREDIENTS: Flurbiprofen 100 mg/1 1
INACTIVE INGREDIENTS: SILICON DIOXIDE; CROSCARMELLOSE SODIUM; HYPROMELLOSE 2910 (3 MPA.S); LACTOSE MONOHYDRATE; MAGNESIUM STEARATE; MICROCRYSTALLINE CELLULOSE; POLYETHYLENE GLYCOL 400; POLYETHYLENE GLYCOL 8000; POLYSORBATE 80; TITANIUM DIOXIDE; FD&C BLUE NO. 1 ALUMINUM LAKE

HIGHLIGHTS OF PRESCRIBING INFORMATION

These highlights do not include all the information needed to use FLURBIPROFEN TABLETS safely and effectively. See full prescribing information for FLURBIPROFEN TABLETS.
FLURBIPROFEN tablets, for oral use
Initial U.S. Approval: 1988

WARNING: RISK OF SERIOUS CARDIOVASCULAR AND GASTROINTESTINAL EVENTS

See full prescribing information for complete boxed warning.

- Nonsteroidal anti-inflammatory drugs (NSAIDs) cause an increased risk of serious cardiovascular thrombotic events, including myocardial infarction and stroke, which can be fatal. This risk may occur early in treatment and may increase with duration of use (5.1)
- Flurbiprofen tablets are contraindicated in the setting of coronary artery bypass graft (CABG) surgery (4, 5.1)
- NSAIDs cause an increased risk of serious gastrointestinal (GI) adverse events including bleeding, ulceration, and perforation of the stomach or intestines, which can be fatal. These events can occur at any time during use and without warning symptoms. Elderly patients and patients with a prior history of peptic ulcer disease and/or GI bleeding are at greater risk for serious GI events (5.2)

1 INDICATIONS AND USAGE

Flurbiprofen tablets are a nonsteroidal anti-inflammatory drug indicated for

- Relief of the signs and symptoms of rheumatoid arthritis (1)
- Relief of the signs and symptoms of osteoarthritis (1)

2 DOSAGE AND ADMINISTRATION

- Use the lowest effective dosage for shortest duration consistent with individual patient treatment goals (2)
- The recommended starting dose of flurbiprofen tablets is 200 to 300 mg per day, divided for administration two, three, or four times a day. The largest recommended single dose in a multiple-dose daily regimen is 100 mg (2)

3 DOSAGE FORMS AND STRENGTHS

Tablets: 100 mg (3)

4 CONTRAINDICATIONS

- Known hypersensitivity to flurbiprofen or any components of the drug product (5.7, 5.9)
- History of asthma, urticaria, or other allergic-type reactions after taking aspirin or other NSAIDs (5.7, 5.8)
- In the setting of CABG surgery (5.1)

5 WARNINGS AND PRECAUTIONS

- Hepatotoxicity: Inform patients of warning signs and symptoms of hepatotoxicity. Discontinue if abnormal liver tests persist or worsen or if clinical signs and symptoms of liver disease develop (5.3)
- Hypertension: Patients taking some antihypertensive medications may have impaired response to these therapies when taking NSAIDs. Monitor blood pressure (5.4, 7)
- Heart Failure and Edema: Avoid use of flurbiprofen in patients with severe heart failure unless benefits are expected to outweigh risk of worsening heart failure (5.5)
- Renal Toxicity: Monitor renal function in patients with renal or hepatic impairment, heart failure, dehydration, or hypovolemia. Avoid use of flurbiprofen in patients with advanced renal disease unless benefits are expected to outweigh risk of worsening renal function (5.6)
- Anaphylactic Reactions: Seek emergency help if an anaphylactic reaction occurs (5.7)
- Exacerbation of Asthma Related to Aspirin Sensitivity: Flurbiprofen is contraindicated in patients with aspirin-sensitive asthma. Monitor patients with preexisting asthma (without aspirin sensitivity) (5.8)
- Serious Skin Reactions: Discontinue flurbiprofen at first appearance of skin rash or other signs of hypersensitivity (5.9)
- Drug Rash with Eosinophilia and Systemic Symptoms (DRESS): Discontinue and evaluate clinically (5.10).
- Fetal Toxicity: Limit use of NSAIDs, including flurbiprofen tablets, between about 20 to 30 weeks in pregnancy due to the risk of oligohydramnios/fetal renal dysfunction. Avoid use of NSAIDs in women at about 30 weeks gestation and later in pregnancy due to the risks of oligohydramnios/fetal renal dysfunction and premature closure of the fetal ductus arteriosus (5.11, 8.1).
- Hematologic Toxicity: Monitor hemoglobin or hematocrit in patients with any signs or symptoms of anemia (5.12, 7)

6 ADVERSE REACTIONS

Most common adverse reactions (incidence > 3% from clinical trials) are: abdominal pain, dyspepsia, nausea, diarrhea, constipation, headache, edema, signs and symptoms suggesting urinary tract infection (6.1)

To report SUSPECTED ADVERSE REACTIONS, contact Allucent at 1-866-511-6754 or FDA at 1-800-FDA-1088 or http://www.fda.gov/medwatch for voluntary reporting of adverse reactions.

7 DRUG INTERACTIONS

- Drugs that Interfere with Hemostasis (e.g. warfarin, aspirin, SSRIs/SNRIs): Monitor patients for bleeding who are concomitantly taking flurbiprofen with drugs that interfere with hemostasis. Concomitant use of flurbiprofen and analgesic doses of aspirin is not generally recommended (7)
- ACE Inhibitors, Angiotensin Receptor Blockers (ARB), or Beta-Blockers: Concomitant use with flurbiprofen may diminish the antihypertensive effect of these drugs. Monitor blood pressure (7)
- ACE Inhibitors and ARBs: Concomitant use with flurbiprofen in elderly, volume depleted, or those with renal impairment may result in deterioration of renal function. In such high risk patients, monitor for signs of worsening renal function (7)
- Diuretics: NSAIDs can reduce natriuretic effect of furosemide and thiazide diuretics. Monitor patients to assure diuretic efficacy including antihypertensive effects (7)

8 USE IN SPECIFIC POPULATIONS

Infertility: NSAIDs are associated with reversible infertility. Consider withdrawal of flurbiprofen in women who have difficulties conceiving (8.3)

FULL PRESCRIBING INFORMATION

WARNING: RISK OF SERIOUS CARDIOVASCULAR AND GASTROINTESTINAL EVENTS

Cardiovascular Thrombotic Events

- Nonsteroidal anti-inflammatory drugs (NSAIDs) cause an increased risk of serious cardiovascular thrombotic events, including myocardial infarction and stroke, which can be fatal. This risk may occur early in treatment and may increase with duration of use [see Warnings and Precautions (5.1)].
- Flurbiprofen tablets are contraindicated in the setting of coronary artery bypass graft (CABG) surgery [see Contraindications (4) and Warnings and Precautions (5.1)].

Gastrointestinal Bleeding, Ulceration, and Perforation

- NSAIDs cause an increased risk of serious gastrointestinal (GI) adverse events including bleeding, ulceration, and perforation of the stomach or intestines, which can be fatal. These events can occur at any time during use and without warning symptoms. Elderly patients and patients with a prior history of peptic ulcer disease and/or GI bleeding are at greater risk for serious GI events [see Warnings and Precautions (5.2)].

1 INDICATIONS AND USAGE

Flurbiprofen tablets are indicated:

- For relief of the signs and symptoms of rheumatoid arthritis.
- For relief of the signs and symptoms of osteoarthritis.

2 DOSAGE AND ADMINISTRATION

Carefully consider the potential benefits and risks of flurbiprofen tablets and other treatment options before deciding to use flurbiprofen tablets. Use the lowest effective dosage for the shortest duration consistent with individual patient treatment goals [see Warnings and Precautions (5)].

After observing the response to initial therapy with flurbiprofen tablets, the dose and frequency should be adjusted to suit an individual patient's needs.

For relief of the signs and symptoms of rheumatoid arthritis or osteoarthritis, the dosage is 200 to 300 mg per day, divided for administration two, three, or four times a day. The largest recommended single dose in a multiple-dose daily regimen is 100 mg.

3 DOSAGE FORMS AND STRENGTHS

Flurbiprofen Tablets, USP: 100 mg round, convex, blue, film-coated tablets debossed "NH" and "100"

4 CONTRAINDICATIONS

Flurbiprofen tablets are contraindicated in the following patients:

- Known hypersensitivity (e.g., anaphylactic reactions and serious skin reactions) to flurbiprofen or any components of the drug product [see Warnings and Precautions (5.7, 5.9)]
- History of asthma, urticaria, or other allergic-type reactions after taking aspirin or other NSAIDs. Severe, sometimes fatal, anaphylactic reactions to nonsteroidal anti-inflammatory drugs have been reported in such patients [see Warnings and Precautions (5.7, 5.8)].
- In the setting of coronary artery bypass graft (CABG) surgery [see Warnings and Precautions (5.1)].

5 WARNINGS AND PRECAUTIONS

5.1 Cardiovascular Thrombotic Events

Clinical trials of several COX-2 selective and nonselective NSAIDs of up to three years duration have shown an increased risk of serious cardiovascular (CV) thrombotic events, including myocardial infarction (MI), and stroke, which can be fatal. Based on available data, it is unclear that the risk for CV thrombotic events is similar for all NSAIDs. The relative increase in serious CV thrombotic events over baseline conferred by NSAID use appears to be similar in those with and without known CV disease or risk factors for CV disease. However, patients with known CV disease or risk factors had a higher absolute incidence of excess serious CV thrombotic events, due to their increased baseline rate. Some observational studies found that this increased risk of serious CV thrombotic events began as early as the first weeks of treatment. The increase in CV thrombotic risk has been observed most consistently at higher doses.

To minimize the potential risk for an adverse CV event in NSAID-treated patients, use the lowest effective dose for the shortest duration possible. Physicians and patients should remain alert for the development of such events, throughout the entire treatment course, even in the absence of previous CV symptoms. Patients should be informed about the symptoms of serious CV events and the steps to take if they occur.

There is no consistent evidence that concurrent use of aspirin mitigates the increased risk of serious CV thrombotic events associated with NSAID use. The concurrent use of aspirin and an NSAID, such as flurbiprofen, increases the risk of serious gastrointestinal (GI) events [see Warnings and Precautions (5.2)].

Status Post Coronary Artery Bypass Graft (CABG) Surgery

Two large, controlled clinical trials of a COX-2 selective NSAID for the treatment of pain in the first 10 to 14 days following CABG surgery found an increased incidence of myocardial infarction and stroke. NSAIDs are contraindicated in the setting of CABG [see Contraindications (4)].

Post-MI Patients

Observational studies conducted in the Danish National Registry have demonstrated that patients treated with NSAIDs in the post-MI period were at increased risk of reinfarction, CV-related death, and all-cause mortality beginning in the first week of treatment. In this same cohort, the incidence of death in the first year post-MI was 20 per 100 person years in NSAID-treated patients compared to 12 per 100 person years in non-NSAID exposed patients. Although the absolute rate of death declined somewhat after the first year post-MI, the increased relative risk of death in NSAID users persisted over at least the next four years of follow-up.

Avoid the use of flurbiprofen in patients with a recent MI unless the benefits are expected to outweigh the risk of recurrent CV thrombotic events. If flurbiprofen is used in patients with a recent MI, monitor patients for signs of cardiac ischemia.

5.2 Gastrointestinal Bleeding, Ulceration, and Perforation

NSAIDs, including flurbiprofen, cause serious gastrointestinal (GI) adverse events including inflammation, bleeding, ulceration, and perforation of the esophagus, stomach, small intestine, or large intestine, which can be fatal. These serious adverse events can occur at any time, with or without warning symptoms, in patients treated with NSAIDs. Only one in five patients, who develop a serious upper GI adverse event on NSAID therapy, is symptomatic. Upper GI ulcers, gross bleeding, or perforation caused by NSAIDs occur in approximately 1% of patients treated for 3 to 6 months, and in about 2% to 4% of patients treated for one year. However, even short-term therapy is not without risk.

Risk Factors for GI Bleeding, Ulceration, and Perforation

Patients with a prior history of peptic ulcer disease and/or GI bleeding who used NSAIDs had a greater than 10-times increased risk for developing a GI bleed compared to patients without these risk factors. Other factors that increase the risk of GI bleeding in patients treated with NSAIDs include longer duration of NSAID therapy; concomitant use of oral corticosteroids, aspirin, anticoagulants, or selective serotonin reuptake inhibitors (SSRIs); smoking, use of alcohol, older age, and poor general health status. Most postmarketing reports of fatal GI events occurred in elderly or debilitated patients. Additionally, patients with advanced liver disease and/or coagulopathy are at increased risk for GI bleeding.

Strategies to Minimize the GI Risks in NSAID-treated patients:

- Use the lowest effective dosage for the shortest possible duration.
- Avoid administration of more than one NSAID at a time.
- Avoid use in patients at higher risk unless benefits are expected to outweigh the increased risk of bleeding. For such patients, as well as those with active GI bleeding, consider alternate therapies other than NSAIDs.
- Remain alert for signs and symptoms of GI ulceration and bleeding during NSAID therapy.
- If a serious GI adverse event is suspected, promptly initiate evaluation and treatment, and discontinue flurbiprofen until a serious GI adverse event is ruled out.
- In the setting of concomitant use of low-dose aspirin for cardiac prophylaxis, monitor patients more closely for evidence of GI bleeding [see Drug Interactions (7)].

5.3 Hepatotoxicity

Elevations of ALT or AST (three or more times the upper limit of normal [ULN]) have been reported in approximately 1% of NSAID-treated patients in clinical trials. In addition, rare, sometimes fatal, cases of severe hepatic injury, including fulminant hepatitis, liver necrosis, and hepatic failure have been reported.

Elevations of ALT or AST (less than three times ULN) may occur in up to 15% of patients treated with NSAIDs including flurbiprofen.

Inform patients of the warning signs and symptoms of hepatotoxicity (e.g., nausea, fatigue, lethargy, diarrhea, pruritus, jaundice, right upper quadrant tenderness, and "flu-like" symptoms). If clinical signs and symptoms consistent with liver disease develop, or if systemic manifestations occur (e.g., eosinophilia, rash, etc.), discontinue flurbiprofen immediately, and perform a clinical evaluation of the patient.

5.4 Hypertension

NSAIDs, including flurbiprofen, can lead to new onset of hypertension or worsening of preexisting hypertension, either of which may contribute to the increased incidence of CV events. Patients taking angiotensin converting enzyme (ACE) inhibitors, thiazide diuretics, or loop diuretics may have impaired response to these therapies when taking NSAIDs [see Drug Interactions (5.1, 7)].

Monitor blood pressure (BP) during the initiation of NSAID treatment and throughout the course of therapy.

5.5 Heart Failure and Edema

The Coxib and traditional NSAID Trialists' Collaboration meta-analysis of randomized controlled trials demonstrated an approximately two-fold increase in hospitalizations for heart failure in COX-2 selective-treated patients and nonselective NSAID-treated patients compared to placebo-treated patients. In a Danish National Registry study of patients with heart failure, NSAID use increased the risk of MI, hospitalization for heart failure, and death.

Additionally, fluid retention and edema have been observed in some patients treated with NSAIDs. Use of flurbiprofen may blunt the CV effects of several therapeutic agents used to treat these medical conditions (e.g., diuretics, ACE inhibitors, or angiotensin receptor blockers [ARBs]) [see Drug Interactions (7)].

Avoid the use of flurbiprofen in patients with severe heart failure unless the benefits are expected to outweigh the risk of worsening heart failure. If flurbiprofen is used in patients with severe heart failure, monitor patients for signs of worsening heart failure.

5.6 Renal Toxicity and Hyperkalemia

Renal Toxicity

Long-term administration of NSAIDs has resulted in renal papillary necrosis and other renal injury.

Renal toxicity has also been seen in patients in whom renal prostaglandins have a compensatory role in the maintenance of renal perfusion. In these patients, administration of an NSAID may cause a dose-dependent reduction in prostaglandin formation and, secondarily, in renal blood flow, which may precipitate overt renal decompensation. Patients at greatest risk of this reaction are those with impaired renal function, dehydration, hypovolemia, heart failure, liver dysfunction, those taking diuretics and ACE inhibitors or ARBs, and the elderly. Discontinuation of NSAID therapy is usually followed by recovery to the pretreatment state.

In clinical studies, the elimination half-life of flurbiprofen was unchanged in patients with renal impairment. Flurbiprofen metabolites are eliminated primarily by the kidneys. Elimination of 4'-hydroxy-flurbiprofen was reduced in patients with moderate to severe renal impairment. Therefore, treatment with flurbiprofen is not recommended in these patients with advanced renal disease. If flurbiprofen therapy must be initiated, close monitoring of the patients renal function is advisable [see Clinical Pharmacology (12)].

Correct volume status in dehydrated or hypovolemic patients prior to initiating flurbiprofen. Monitor renal function in patients with renal or hepatic impairment, heart failure, dehydration, or hypovolemia during use of flurbiprofen [see Drug Interactions (7)]. Avoid the use of flurbiprofen in patients with advanced renal disease unless the benefits are expected to outweigh the risk of worsening renal function. If flurbiprofen is used in patients with advanced renal disease, monitor patients for signs of worsening renal function.

Hyperkalemia

Increases in serum potassium concentration, including hyperkalemia, have been reported with use of NSAIDs even in some patients without renal impairment. In patients with normal renal function, these effects have been attributed to a hyporeninemic-hypoaldosteronism state.

5.7 Anaphylactic Reactions

Flurbiprofen has been associated with anaphylactic reactions in patients with and without known hypersensitivity to flurbiprofen and in patients with aspirin-sensitive asthma [see Contraindications (4) and Warnings and Precautions (5.8)].

Seek emergency help if an anaphylactic reaction occurs.

5.8 Exacerbation of Asthma Related to Aspirin Sensitivity

A subpopulation of patients with asthma may have aspirin-sensitive asthma which may include chronic rhinosinusitis complicated by nasal polyps; severe, potentially fatal bronchospasm; and/or intolerance to aspirin and other NSAIDs. Because cross-reactivity between aspirin and other NSAIDs has been reported in such aspirin-sensitive patients, flurbiprofen is contraindicated in patients with this form of aspirin sensitivity [see Contraindications (4)]. When flurbiprofen is used in patients with preexisting asthma (without known aspirin sensitivity), monitor patients for changes in the signs and symptoms of asthma.

5.9 Serious Skin Reactions

NSAIDs, including flurbiprofen, can cause serious skin adverse reactions such as exfoliative dermatitis, Stevens-Johnson Syndrome (SJS), and toxic epidermal necrolysis (TEN), which can be fatal. These serious events may occur without warning. Inform patients about the signs and symptoms of serious skin reactions, and to discontinue the use of flurbiprofen at the first appearance of skin rash or any other sign of hypersensitivity. Flurbiprofen is contraindicated in patients with previous serious skin reactions to NSAIDs [see Contraindications (4)].

5.10 Drug Rash with Eosinophilia and Systemic Symptoms (DRESS)

Drug Reaction with Eosinophilia and Systemic Symptoms (DRESS) has been reported in patients taking NSAIDs such as flurbiprofen tablets. Some of these events have been fatal or life-threatening. DRESS typically, although not exclusively, presents with fever, rash, lymphadenopathy, and/or facial swelling. Other clinical manifestations may include hepatitis, nephritis, hematological abnormalities, myocarditis, or myositis. Sometimes symptoms of DRESS may resemble an acute viral infection. Eosinophilia is often present. Because this disorder is variable in its presentation, other organ systems not noted here may be involved. It is important to note that early manifestations of hypersensitivity, such as fever or lymphadenopathy, may be present even though rash is not evident. If such signs or symptoms are present, discontinue flurbiprofen tablets and evaluate the patient immediately.

5.11 Fetal Toxicity

Premature Closure of Fetal Ductus Arteriosus:

Avoid use of NSAIDs, including flurbiprofen tablets, in pregnant women at about 30 weeks gestation and later. NSAIDs, including flurbiprofen tablets, increase the risk of premature closure of the fetal ductus arteriosus at approximately this gestational age.

Oligohydramnios/Neonatal Renal Impairment:

Use of NSAIDs, including flurbiprofen tablets, at about 20 weeks gestation or later in pregnancy may cause fetal renal dysfunction leading to oligohydramnios and, in some cases, neonatal renal impairment. These adverse outcomes are seen, on average, after days to weeks of treatment, although oligohydramnios has been infrequently reported as soon as 48 hours after NSAID initiation. Oligohydramnios is often, but not always, reversible with treatment discontinuation. Complications of prolonged oligohydramnios may, for example, include limb contractures and delayed lung maturation. In some postmarketing cases of impaired neonatal renal function, invasive procedures such as exchange transfusion or dialysis were required.

If NSAID treatment is necessary between about 20 weeks and 30 weeks gestation, limit flurbiprofen tablets use to the lowest effective dose and shortest duration possible. Consider ultrasound monitoring of amniotic fluid if flurbiprofen tablets treatment extends beyond 48 hours. Discontinue flurbiprofen tablets if oligohydramnios occurs and follow up according to clinical practice [see Use in Specific Populations (8.1)].

5.12 Hematologic Toxicity

Anemia has occurred in NSAID-treated patients. This may be due to occult or gross blood loss, fluid retention, or an incompletely described effect on erythropoiesis. If a patient treated with flurbiprofen has any signs or symptoms of anemia, monitor hemoglobin or hematocrit.

NSAIDs, including flurbiprofen, may increase the risk of bleeding events. Co-morbid conditions such as coagulation disorders of concomitant use of warfarin, other anticoagulants, antiplatelet agents (e.g., aspirin), serotonin reuptake inhibitors (SSRIs), and serotonin norepinephrine reuptake inhibitors (SNRIs) may increase this risk. Monitor these patients for signs of bleeding [see Drug Interactions (7)].

5.13 Masking of Inflammation and Fever

The pharmacological activity of flurbiprofen in reducing inflammation, and possibly fever, may diminish the utility of diagnostic signs in detecting infections.

5.14 Laboratory Monitoring

Because serious GI bleeding, hepatotoxicity, and renal injury can occur without warning symptoms or signs, consider monitoring patients on long-term NSAID treatment with a CBC and a chemistry profile periodically [see Warnings and Precautions (5.2, 5.3, 5.6)].

5.15 Vision Changes

Blurred and/or diminished vision has been reported with the use of flurbiprofen and other nonsteroidal anti-inflammatory drugs. Patients experiencing eye complaints should have ophthalmologic examinations.

6 ADVERSE REACTIONS

The following adverse reactions are discussed in greater detail in other sections of the labeling:

- Cardiovascular Thrombotic Events [see Warnings and Precautions (5.1)]
- GI Bleeding, Ulceration and Perforation [see Warnings and Precautions (5.2)]
- Hepatotoxicity [see Warnings and Precautions (5.3)]
- Hypertension [see Warnings and Precautions (5.4)]
- Heart Failure and Edema [see Warnings and Precautions (5.5)]
- Renal Toxicity and Hyperkalemia [see Warnings and Precautions (5.6)]
- Anaphylactic Reactions [see Warnings and Precautions (5.7)]
- Serious Skin Reactions [see Warnings and Precautions (5.9)]
- Hematologic Toxicity [see Warnings and Precautions (5.12)]

6.1 Clinical Trials Experience

Because clinical trials are conducted under widely varying conditions, adverse reaction rates observed in the clinical trials of a drug cannot be directly compared to rates in the clinical trials of another drug and may not reflect the rates observed in practice.

Incidence of 1% or greater

Body as a whole: edema

Digestive system: GI bleeding, abdominal pain, constipation, diarrhea, dyspepsia/heartburn, flatulence, nausea, vomiting, elevated liver enzymes

Metabolic and nutritional system: body weight changes

Nervous system: headache, nervousness, anxiety, insomnia, increased reflexes, tremor, amnesia, asthenia, depression, malaise, somnolence

Respiratory system: rhinitis

Skin and appendages: rash

Special senses: changes in vision, dizziness, tinnitus

Urogenital system: signs and symptoms suggesting urinary tract infection

Incidence < 1 %

Body as a whole: anaphylactic reaction, chills, fever

Cardiovascular system: myocardial infarction, congestive heart failure, hypertension, vascular diseases, vasodilation

Digestive system: gastric/peptic ulcer disease, hematemesis, bloody diarrhea, hepatitis, esophageal disease, gastritis, stomatitis/glossitis, dry mouth

Hemic and lymphatic system: iron deficiency anemia, decrease in hemoglobin and hematocrit, purpura, eosinophilia

Metabolic and nutritional system: hyperuricemia

Nervous system: cerebrovascular ischemia, convulsion, ataxia, confusion, hypertonia, paresthesia, twitching, emotional lability

Respiratory system: asthma, dyspnea, epistaxis, bronchitis, laryngitis

Skin and appendages: angioedema, urticaria, eczema, pruritus, herpes simplex, alopecia, dry skin

Special senses: vertigo, corneal opacity, parosmia, conjunctivitis

Urogenital system: renal failure, vaginal hemorrhage, hematuria

6.2 Postmarketing Experience

The following adverse reactions have been identified during post approval use of flurbiprofen. Because these reactions are reported voluntarily from a population of uncertain size, it is not always possible to reliably estimate their frequency or establish a causal relationship to drug exposure.

Cardiovascular system: angina pectoris, arrhythmias

Digestive system: jaundice (cholestatic and noncholestatic), colitis, small intestine inflammation with loss of blood and protein, exacerbation of inflammatory bowel disease, cholecystitis, periodontal abscess, appetite changes

Hemic and lymphatic system: aplastic anemia (including agranulocytosis or pancytopenia), hemolytic anemia, leukopenia, thrombocytopenia, ecchymosis, lymphadenopathy

Metabolic and nutritional system: hyperkalemia

Nervous system: cerebrovascular accident, subarachnoid hemorrhage, meningitis, myasthenia

Respiratory system: pulmonary infarct, pulmonary embolism, hyperventilation,

Skin and appendages: toxic epidermal necrolysis, exfoliative dermatitis, zoster, photosensitivity, nail disorder, sweating

Special senses: retinal hemorrhage, glaucoma, retrobulbar neuritis, transient hearing loss, changes in taste, ear disease

Urogenital system: interstitial nephritis, uterine hemorrhage, menstrual disturbances, prostate disease, vulvovaginitis

7 DRUG INTERACTIONS

See Table 1 for clinically significant drug interactions with flurbiprofen.

Table 1: Clinically Significant Drug Interactions with Flurbiprofen
Drugs That Interfere with Hemostasis
Clinical Impact: | - Flurbiprofen and anticoagulants such as warfarin have a synergistic effect on bleeding. The concomitant use of flurbiprofen and anticoagulants have an increased risk of serious bleeding compared to the use of either drug alone. - Serotonin release by platelets plays an important role in hemostasis. Case-control and cohort epidemiological studies showed that concomitant use of drugs that interfere with serotonin reuptake and an NSAID may potentiate the risk of bleeding more than an NSAID alone.
Intervention: | Monitor patients with concomitant use of flurbiprofen with anticoagulants (e.g., warfarin), antiplatelet agents (e.g., aspirin), selective serotonin reuptake inhibitors (SSRIs), and serotonin norepinephrine reuptake inhibitors (SNRIs) for signs of bleeding [see Warnings and Precautions (5)].
Aspirin
Clinical Impact: | Controlled clinical studies showed that the concomitant use of NSAIDs and analgesic doses of aspirin does not produce any greater therapeutic effect than the use of NSAIDs alone. In a clinical study, the concomitant use of an NSAID and aspirin was associated with a significantly increased incidence of GI adverse reactions as compared to use of the NSAID alone [see Warnings and Precautions (5)]. Concurrent administration of aspirin lowers serum flurbiprofen concentrations. The clinical significance of this interaction is not known.
Intervention: | Concomitant use of flurbiprofen and analgesic doses of aspirin is not generally recommended because of the increased risk of bleeding [see Warnings and Precautions (5)]. Flurbiprofen is not a substitute for low dose aspirin for cardiovascular protection.
ACE Inhibitors, Angiotensin Receptor Blockers, and Beta-Blockers
Clinical Impact: | - NSAIDs may diminish the antihypertensive effect of angiotensin converting enzyme (ACE) inhibitors, angiotensin receptor blockers (ARBs), or beta-blockers (including propranolol). - In patients who are elderly, volume-depleted (including those on diuretic therapy), or have renal impairment, coadministration of an NSAID with ACE inhibitors or ARBs may result in deterioration of renal function, including possible acute renal failure. These effects are usually reversible.
Intervention: | - During concomitant use of flurbiprofen and ACE-inhibitors, ARBs, or beta-blockers, monitor blood pressure to ensure that the desired blood pressure is obtained. - During concomitant use of flurbiprofen and ACE-inhibitors or ARBs in patients who are elderly, volume-depleted, or have impaired renal function, monitor for signs of worsening renal function [see Warnings and Precautions (5.6)]. - When drugs are administered concomitantly, patients should be adequately hydrated. Assess renal function at the beginning of the concomitant treatment and periodically thereafter.
Diuretics
Clinical Impact: | Clinical studies, as well as post-marketing observations, showed that NSAIDs reduced the natriuretic effect of loop diuretics (e.g., furosemide) and thiazide diuretics in some patients. This effect has been attributed to the NSAID inhibition of renal prostaglandin synthesis.
Intervention: | During concomitant use of flurbiprofen with diuretics, observe patients for signs of worsening renal function, in addition to assuring diuretic efficacy including antihypertensive effects [see Warnings and Precautions (5)].
Digoxin
Clinical Impact: | The concomitant use of flurbiprofen with digoxin has been reported to increase the serum concentration and prolong the half-life of digoxin [see Clinical Pharmacology (12.3)].
Intervention: | During concomitant use of flurbiprofen and digoxin, monitor serum digoxin levels.
Lithium
Clinical Impact: | NSAIDs have produced elevations in plasma lithium levels and reductions in renal lithium clearance. The mean minimum lithium concentration increased 15%, and the renal clearance decreased by approximately 20%. This effect has been attributed to NSAID inhibition of renal prostaglandin synthesis.
Intervention: | During concomitant use of flurbiprofen and lithium, monitor patients for signs of lithium toxicity.
Methotrexate
Clinical Impact: | Concomitant use of NSAIDs and methotrexate may increase the risk for methotrexate toxicity (e.g., neutropenia, thrombocytopenia, renal dysfunction).
Intervention: | During concomitant use of flurbiprofen and methotrexate, monitor patients for methotrexate toxicity.
Cyclosporine
Clinical Impact: | Concomitant use of flurbiprofen and cyclosporine may increase cyclosporine's nephrotoxicity.
Intervention: | During concomitant use of flurbiprofen and cyclosporine, monitor patients for signs of worsening renal function.
NSAIDs and Salicylates
Clinical Impact: | Concomitant use of flurbiprofen with other NSAIDs or salicylates (e.g., diflunisal, salsalate) increases the risk of GI toxicity, with little or no increase in efficacy [see Warnings and Precautions (5.2)].
Intervention: | The concomitant use of flurbiprofen with other NSAIDs or salicylates is not recommended.
Pemetrexed
Clinical Impact: | Concomitant use of flurbiprofen and pemetrexed may increase the risk of pemetrexed-associated myelosuppression, renal, and GI toxicity (see the pemetrexed prescribing information).
Intervention: | During concomitant use of flurbiprofen and pemetrexed, in patients with renal impairment whose creatinine clearance ranges from 45 to 79 mL/min, monitor for myelosuppression, renal and GI toxicity. NSAIDs with short elimination half-lives (e.g., diclofenac, indomethacin) should be avoided for a period of two days before, the day of, and two days following administration of pemetrexed. In the absence of data regarding potential interaction between pemetrexed and NSAIDs with longer half-lives (e.g., meloxicam, nabumetone), patients taking these NSAIDs should interrupt dosing for at least five days before, the day of, and two days following pemetrexed administration.
Corticosteroids
Clinical Impact: | Concomitant use of corticosteroids with flurbiprofen may increase the risk of GI ulceration or bleeding.
Intervention: | Monitor patients with concomitant use of flurbiprofen with corticosteroids for signs of bleeding [see Warnings and Precautions (5.2)].

8 USE IN SPECIFIC POPULATIONS

8.1 Pregnancy

Risk Summary

Use of NSAIDs, including flurbiprofen tablets, can cause premature closure of the fetal ductus arteriosus and fetal renal dysfunction leading to oligohydramnios and, in some cases, neonatal renal impairment. Because of these risks, limit dose and duration of flurbiprofen tablets use between about 20 and 30 weeks of gestation, and avoid flurbiprofen tablets use at about 30 weeks of gestation and later in pregnancy [see Clinical Considerations, Data].

Premature Closure of Fetal Ductus Arteriosus

Use of NSAIDs, including flurbiprofen tablets, at about 30 weeks gestation or later in pregnancy increases the risk of premature closure of the fetal ductus arteriosus.

Oligohydramnios/Neonatal Renal Impairment

Use of NSAIDs at about 20 weeks gestation or later in pregnancy has been associated with cases of fetal renal dysfunction leading to oligohydramnios, and in some cases, neonatal renal impairment.

Data from observational studies regarding potential embryofetal risks of NSAID use in U.S. population, all clinically recognized pregnancies, regardless of drug exposure, women in the first or second trimesters of pregnancy are inconclusive. In the general have a background rate of 2 to 4% for major malformations, and 15 to 20% for pregnancy loss. In animal reproduction studies, delayed parturition, prolonged labor, stillborn fetuses, and the presence of retained fetuses at necropsy occurred following treatment of pregnant rats treated with oral flurbiprofen throughout gestation until labor at less than 1-time the human dose of 300 mg/day. Embryofetal lethality was seen in pregnant rats and rabbits administered oral flurbiprofen during the period of organogenesis at exposures 0.03-times and 0.5 times, respectively, the human dose of 300 mg. No evidence of malformations were noted in rats, rabbits, or mice treated with flurbiprofen during the period of organogenesis at doses that were 0.8-, 0.5-, and 0.2-times the maximum human daily dose [see Data]. Based on animal data, prostaglandins have been shown to have an important role in endometrial vascular permeability, blastocyst implantation, and decidualization. In animal studies, administration of prostaglandin synthesis inhibitors such as flurbiprofen, resulted in increased pre- and post-implantation loss. Prostaglandins also have been shown to have an important role in fetal kidney development. In published animal studies, prostaglandin synthesis inhibitors have been reported to impair kidney development when administered at clinically relevant doses.

Clinical Considerations

Fetal/Neonatal Adverse Reactions

Premature Closure of Fetal Ductus Arteriosus:

Avoid use of NSAIDs in women at about 30 weeks gestation and later in pregnancy, because NSAIDs, including flurbiprofen tablets, can cause premature closure of the fetal ductus arteriosus [see Data].

Oligohydramnios/Neonatal Renal Impairment

If an NSAID is necessary at about 20 weeks gestation or later in pregnancy, limit the use to the lowest effective dose and shortest duration possible. If flurbiprofen tablets treatment extends beyond 48 hours, consider monitoring with ultrasound for oligohydramnios. If oligohydramnios occurs, discontinue flurbiprofen tablets and follow up according to clinical practice [see Data].

Data

Human Data

Premature Closure of Fetal Ductus Arteriosus:

Published literature reports that the use of NSAIDs at about 30 weeks of gestation and later in pregnancy may cause premature closure of the fetal ductus arteriosus.

Oligohydramnios/Neonatal Renal Impairment:

Published studies and postmarketing reports describe maternal NSAID use at about 20 weeks gestation or later in pregnancy associated with fetal renal dysfunction leading to oligohydramnios, and in some cases, neonatal renal impairment. These adverse outcomes are seen, on average, after days to weeks of treatment, although oligohydramnios has been infrequently reported as soon as 48 hours after NSAID initiation. In many cases, but not all, the decrease in amniotic fluid was transient and reversible with cessation of the drug. There have been a limited number of case reports of maternal NSAID use and neonatal renal dysfunction without oligohydramnios, some of which were irreversible. Some cases of neonatal renal dysfunction required treatment with invasive procedures, such as exchange transfusion or dialysis.

Methodological limitations of these postmarketing studies and reports include lack of a control group; limited information regarding dose, duration, and timing of drug exposure; and concomitant use of other medications. These limitations preclude establishing a reliable estimate of the risk of adverse fetal and neonatal outcomes with maternal NSAID use. Because the published safety data on neonatal outcomes involved mostly preterm infants, the generalizability of certain reported risks to the full-term infant exposed to NSAIDs through maternal use is uncertain.

Animal data

Pregnant rats were treated with oral doses of 0.05, 1, and 3 mg/kg flurbiprofen 14 days prior to mating through Gestation Day (GD) 16. Embryofetal lethality was seen at 1 mg/kg and above (0.03 times the maximum recommended human dose [MRHD] of 300 mg on a mg/m^2 basis). No maternal toxicity was evident at this dose. No malformations were seen in fetuses from pregnant rats administered flurbiprofen during the period of organogenesis at doses up to 25 mg/kg (0.8 times the MRHD on a mg/m^2 basis). Maternal toxicity (uterine hemorrhage, gastric ulcers) was observed at this dose.

Pregnant rabbits were administered oral doses of 0.675, 2.25, and 7.5 mg/kg flurbiprofen from GD 1 through GD 29. Embryofetal lethality, but no evidence of teratogenicity, was seen at 7.5 mg/kg (0.5 times the MRHD of 300 mg on a mg/m^2 basis). Maternal toxicity (gastric ulcers and lethality) was observed at this dose.

Pregnant mice were treated with oral doses of 2, 5, and 12 mg/kg flurbiprofen from GD 3 to 18. An increased incidence of fetal lethality occurred in the 12 mg/kg group (0.2 times the MRHD). All doses were associated with some evidence of maternal toxicity (placental hemorrhage).

Pregnant rats were treated with oral doses of 0.2, 0.675, 2.25, 7.5, and 25 mg/kg flurbiprofen from GD 1 until labor. Delayed delivery, the incidence of stillborn pups, and decreased pup viability, were noted at doses of 2.25 mg/kg and higher (0.07 times the MRHD). These doses were associated with maternal toxicity (uterine hemorrhage, gastrointestinal ulceration, decreased body weight).

Pregnant rats treated with oral doses of 0.4, 4, and 10 mg/kg flurbiprofen from GD 16 to labor, delayed parturition was seen at 0.4 mg/kg and above and stillborn pups were seen at 4 mg/kg and above (0.01-times and 0.13 times, respectively, the MRHD on mg/m^2 basis). Uterine hemorrhage, ulceration, and mortality were noted in dams at 0.4 mg/kg and above.

Labor or Delivery

There are no studies on the effects of flurbiprofen during labor or delivery. In animal studies, NSAIDS, including flurbiprofen, inhibit prostaglandin synthesis, cause delayed parturition, and increase the incidence of stillbirth.

8.2 Lactation

Risk Summary

Flurbiprofen is poorly excreted into human milk. The nursing infant dose is predicted to be approximately 0.1 mg/day in the established milk of a woman taking flurbiprofen 200 mg/day. The developmental and health benefits of breastfeeding should be considered along with the mother's clinical need for flurbiprofen and any potential adverse effects on the breastfed infant from flurbiprofen or from the underlying maternal condition.

8.3 Females and Males of Reproductive Potential

Infertility

Females

Based on the mechanism of action, the use of prostaglandin-mediated NSAIDs, including flurbiprofen, may delay or prevent rupture of ovarian follicles, which has been associated with reversible infertility in some women. Published animal studies have shown that administration of prostaglandin synthesis inhibitors has the potential to disrupt prostaglandin-mediated follicular rupture required for ovulation. Small studies in women treated with NSAIDs have also shown a reversible delay in ovulation. Consider withdrawal of NSAIDs, including flurbiprofen, in women who have difficulties conceiving or who are undergoing investigation of infertility.

8.4 Pediatric Use

Safety and effectiveness in pediatric patients have not been established.

8.5 Geriatric Use

Elderly patients, compared to younger patients, are at greater risk for NSAID-associated serious cardiovascular, gastrointestinal, and/or renal adverse reactions. If the anticipated benefit for the elderly patient outweighs these potential risks, start dosing at the low end of the dosing range, and monitor patients for adverse effects [see Warnings and Precautions (5.1, 5.2, 5.3, 5.6, 5.14)].

10 OVERDOSAGE

Symptoms following acute NSAID overdosages have been typically limited to lethargy, drowsiness, nausea, vomiting, and epigastric pain, which are generally reversible with supportive care. Gastrointestinal bleeding has occurred. Hypertension, acute renal failure, respiratory depression and coma have occurred, but were rare [see Warnings and Precautions (5.1, 5.2, 5.4, 5.6)].

Manage patients with symptomatic and supportive care following an NSAID overdosage. There are no specific antidotes. Consider emesis and/or activated charcoal (60 to 100 grams in adults, 1 to 2 grams per kg of body weight in pediatric patients) and/or osmotic cathartic in symptomatic patients seen within four hours of ingestion or in patients with a large overdosage (5 to 10 times the recommended dosage). Forced diuresis, alkalinization of urine, hemodialysis, or hemoperfusion may not be useful due to high protein binding.

For additional information about overdosage treatment contact a poison control center (1-800-222-1222).

11 DESCRIPTION

Flurbiprofen Tablets, USP are a member of the phenylalkanoic acid derivative group of nonsteroidal anti-inflammatory drug. Flurbiprofen Tablets, USP are round, blue, film-coated debossed "NH" – "100" tablets for oral administration. Flurbiprofen, USP is a racemic mixture of (+)S- and (-)R- enantiomers. Flurbiprofen, USP is a white or slightly yellow crystalline powder. It is slightly soluble in water at pH 7.0 and readily soluble in most polar solvents. The chemical name is [1,1'-biphenyl]-4-acetic acid, 2-fluoro-α-methyl-, (±)-. It has the following structural formula:

C15H13FO2 M.W. 244.26

Each tablet, for oral administration, contains 100 mg flurbiprofen, USP. In addition, each tablet contains the following inactive ingredients: colloidal silicon dioxide, croscarmellose sodium, hypromellose, lactose monohydrate, magnesium stearate, microcrystalline cellulose, polyethylene glycol, polysorbate 80, titanium dioxide, and FD&C Blue #1 aluminum lake.

12 CLINICAL PHARMACOLOGY

12.1 Mechanism of Action

Flurbiprofen has analgesic, anti-inflammatory, and antipyretic properties.

The mechanism of action of flurbiprofen, like that of other NSAIDs, is not completely understood but involves inhibition of cyclooxygenase (COX-1 and COX-2).

Flurbiprofen is a potent inhibitor of prostaglandin (PG) synthesis in vitro. Flurbiprofen concentrations reached during therapy have produced in vivo effects. Prostaglandins sensitize afferent nerves and potentiate the action of bradykinin in inducing pain in animal models. Prostaglandins are mediators of inflammation. Because flurbiprofen is an inhibitor of prostaglandin synthesis, its mode of action may be due to a decrease of prostaglandins in peripheral tissues.

12.3 Pharmacokinetics

General pharmacokinetic characteristics

The pharmacokinetics of flurbiprofen have been characterized in healthy subjects, special populations and patients (see Table 2). The pharmacokinetics of flurbiprofen are linear, and there is little accumulation of flurbiprofen following multiple doses of flurbiprofen.

Table 2 :Mean (SD) R-, S-Flurbiprofen Pharmacokinetic Parameters Normalized to a 100 mg Dose of Flurbiprofen Tablets
Pharmacokinetic Parameter | Normal Healthy Adults [100 mg single-dose] (18 to 40 years) N = 15 | Geriatric Arthritis Patients [Steady-state evaluation of 100 mg every 12 hours] (65 to 83 years) N = 13 | End Stage Renal Disease Patients (23 to 42 years) N = 8 | Alcoholic Cirrhosis Patients [200 mg single-dose] (31 to 61 years) N = 8
Peak Concentration (mcg/mL) | 14 (4) | 16 (5) | 9 [Calculated from mean parameter values of both flurbiprofen enantiomers] | 9
Time to Reach Peak Concentration (h) | 1.9 (1.5) | 2.2 (3) | 2.3 | 1.2
Urinary Recovery of Unchanged Flurbiprofen (% of Dose) | 2.9 (1.3) | 0.6 (0.6) | 0.02 (0.02) | NA [Not available]
Area Under the Curve (AUC) (mcg∙h/mL) [AUC from 0 to infinity for single doses and from 0 to the end of the dosing interval for multiple-doses] | 83 (20) | 77 (24) | 44 | 50
Apparent Volume of Distribution (Vz/F, L) | 14 (3) | 12 (5) | 10 | 14
Terminal Elimination Half-life (t½, h) | 7.5 (0.8) | 5.8 (1.9) | 3.3 [Value for S-flurbiprofen] | 5.4

Absorption

The mean oral bioavailability of flurbiprofen from flurbiprofen tablets 100 mg is 96% relative to an oral solution. Flurbiprofen is rapidly and non-stereoselectively absorbed from flurbiprofen, with peak plasma concentrations occurring at approximately 2 hours (see Table 2).

Administration of flurbiprofen with either food or antacids may alter the rate but not the extent of flurbiprofen absorption. Ranitidine has been shown to have no effect on either the rate or extent of flurbiprofen absorption from flurbiprofen.

Distribution

The apparent volume of distribution (Vz/F) of both R- and S-flurbiprofen is approximately 0.12 L/kg. Both flurbiprofen enantiomers are more than 99% bound to plasma proteins, primarily albumin. Plasma protein binding is relatively constant for the typical average steady-state concentrations (≤ 10 mcg/mL) achieved with recommended doses. Flurbiprofen is poorly excreted into human milk. The nursing infant dose is predicted to be approximately 0.1 mg/day in the established milk of a woman taking flurbiprofen 200 mg/day.

Metabolism

Several flurbiprofen metabolites have been identified in human plasma and urine. These metabolites include 4'-hydroxy-flurbiprofen, 3', 4'-dihydroxy-flurbiprofen, 3'-hydroxy-4'-methoxy-flurbiprofen, their conjugates, and conjugated flurbiprofen. Unlike other arylpropionic acid derivatives (e.g., ibuprofen), metabolism of R-flurbiprofen to S-flurbiprofen is minimal.

In vitro studies have demonstrated that cytochrome CYP2C9 plays an important role in the metabolism of flurbiprofen to its major metabolite 4'-hydroxy-flurbiprofen. The 4'-hydroxy-flurbiprofen metabolite showed little anti-inflammatory activity in animal models of inflammation. In vitro studies also demonstrated glucuronidation of both enantiomers of flurbiprofen and 4'-hydroxy-flurbiprofen. UGT2B7 is the predominant UGT isozyme responsible for the glucuronidation. Flurbiprofen does not induce enzymes that alter its metabolism.

Excretion

Following dosing with flurbiprofen, less than 3% of flurbiprofen is excreted unchanged in the urine, with about 70% of the dose eliminated in the urine as flurbiprofen, 4'-hydroxy-flurbiprofen, and their acylglucuronide conjugates. Because renal elimination is a significant pathway of elimination of flurbiprofen metabolites, dosing adjustment in patients with moderate or severe renal dysfunction may be necessary to avoid accumulation of flurbiprofen metabolites.

The mean terminal elimination half-lives (t½) of R- and S-flurbiprofen are similar, about 4.7 and 5.7 hours, respectively.

Specific Populations

Pediatric: The pharmacokinetics of flurbiprofen have not been investigated in pediatric patients.

Race: No pharmacokinetic differences due to race have been identified.

Geriatric: Flurbiprofen pharmacokinetics were similar in geriatric arthritis patients, younger arthritis patients, and young healthy volunteers receiving flurbiprofen 100 mg as either single or multiple doses.

Hepatic Impairment: Hepatic metabolism may account for > 90% of flurbiprofen elimination, so patients with hepatic disease may require reduced doses of flurbiprofen compared to patients with normal hepatic function. The pharmacokinetics of R- and S-flurbiprofen were similar, however, in alcoholic cirrhosis patients (N = 8) and young healthy volunteers (N = 8) following administration of a single 200 mg dose of flurbiprofen. Flurbiprofen plasma protein binding may be decreased in patients with liver disease and serum albumin concentrations below 3.1 g/dL.

Renal Impairment: Renal clearance is an important route of elimination for flurbiprofen metabolites, but a minor route of elimination for unchanged flurbiprofen (≤ 3% of total clearance). The unbound clearances of R- and S-flurbiprofen did not differ significantly between normal healthy volunteers (N = 6, 50 mg single dose) and patients with renal impairment (N = 8, inulin clearances ranging from 11 to 43 mL/min, 50 mg multiple doses). Flurbiprofen plasma protein binding may be decreased in patients with renal impairment and serum albumin concentrations below 3.9 g/dL. Elimination of flurbiprofen metabolites may be reduced in patients with renal impairment.

Flurbiprofen is not significantly removed from the blood into dialysate in patients undergoing continuous ambulatory peritoneal dialysis.

Drug Interaction Studies

Antacids:

Administration of flurbiprofen to volunteers under fasting conditions or with antacid suspension yielded similar serum flurbiprofen-time profiles in young adult subjects (n = 12). In geriatric subjects (n = 7), there was a reduction in the rate but not the extent of flurbiprofen absorption.

Aspirin:

Concurrent administration of flurbiprofen and aspirin resulted in 50% lower serum flurbiprofen concentrations. This effect of aspirin (which is also seen with other NSAIDs) has been demonstrated in patients with rheumatoid arthritis (n = 15) and in healthy volunteers (n = 16) [see Drug Interactions (7)].

Beta-adrenergic Blocking Agents:

The effect of flurbiprofen on blood pressure response to propranolol and atenolol was evaluated in men with mild uncomplicated hypertension (n = 10). Flurbiprofen pretreatment attenuated the hypotensive effect of a single dose of propranolol but not atenolol. Flurbiprofen did not appear to affect the beta-blocker-mediated reduction in heart rate. Flurbiprofen did not affect the pharmacokinetic profile of either drug [see Drug Interactions (7)].

Cimetidine, Ranitidine:

In normal volunteers (n = 9), pretreatment with cimetidine or ranitidine did not affect flurbiprofen pharmacokinetics, except for a small (13%) but statistically significant increase in the area under the serum concentration curve of flurbiprofen in subjects who received cimetidine.

Digoxin:

In studies of healthy males (n = 14), concomitant administration of flurbiprofen and digoxin did not change the steady state serum levels of either drug [see Drug Interactions (7)].

Diuretics:

Studies in healthy volunteers have shown that, like other NSAIDs, flurbiprofen can interfere with the effects of furosemide. Although results have varied from study to study, effects have been shown on furosemide-stimulated diuresis, natriuresis, and kaliuresis [see Drug Interactions (7)].

Lithium:

In a study of 11 women with bipolar disorder receiving lithium carbonate at a dosage of 600 to 1200 mg/day, administration of 100 mg flurbiprofen every 12 hours increased plasma lithium concentrations by 19%. Four of 11 patients experienced a clinically important increase (> 25% or > 0.2 mmol/L) [see Drug Interactions (7)].

Methotrexate:

In a study of six adult arthritis patients, coadministration of methotrexate (10 to 25 mg/dose) and flurbiprofen (300 mg/day) resulted in no observable interaction between these two drugs [see Drug Interactions (7)].

Oral Hypoglycemic Agents:

In a clinical study, flurbiprofen was administered to adult diabetics who were already receiving glyburide (n = 4), metformin (n = 2), chlorpropamide with phenformin (n=3), or glyburide with phenformin (n = 6). Although there was a slight reduction in blood sugar concentrations during concomitant administration of flurbiprofen and hypoglycemic agents, there were no signs or symptoms of hypoglycemia.

Poor Metabolizers of CYP2C9 Substrates:

In patients who are known or suspected to be poor CYP2C9 metabolizers based on genotype or previous history/experience with other CYP2C9 substrates (such as warfarin and phenytoin), reduce the dose of flurbiprofen to avoid abnormally high plasma levels due to reduced metabolic clearance.

13 NONCLINICAL TOXICOLOGY

13.1 Carcinogenesis, Mutagenesis, Impairment of Fertility

Carcinogenesis

Flurbiprofen was not carcinogenic in long-term studies in Fischer-344 and CD rats at doses up to 5 mg/kg/day and in CFLP mice at doses up to 12 mg/kg/day (0.16-times and 0.19-times, respectively, the human dose of 300 mg/day on a mg/m^2 basis).

Mutagenesis

Flurbiprofen was not genotoxic in an in vivo micronucleus assay in rats.

Impairment of Fertility

No effect on male or female fertility in rats was observed after oral administration of 3 mg/kg flurbiprofen for 65 days prior to mating in males and 14 days prior to mating through Gestation Day 16 in females (equivalent to 0.1-times the human dose of 300 mg/day on a mg/m^2 basis). This dose was not associated with significant toxicity in the dams or sires.

16 HOW SUPPLIED/STORAGE AND HANDLING

Flurbiprofen Tablets USP, 100 mg are round, convex, blue, film-coated tablets debossed "NH" and "100" available in bottles of 100 (NDC 64950-218-10).

STORAGE AND HANDLING

Store at 20° to 25°C (68° to 77°F) [see USP Controlled Room Temperature].

Dispense in a tight, light-resistant container as defined in the USP, with a child-resistant closure (as required).

17 PATIENT COUNSELING INFORMATION

Advise the patient to read the FDA-approved patient labeling (Medication Guide) that accompanies each prescription dispensed. Inform patients, families, or their caregivers of the following information before initiating therapy with flurbiprofen and periodically during the course of ongoing therapy.

Cardiovascular Thrombotic Events

Advise patients to be alert for the symptoms of cardiovascular thrombotic events, including chest pain, shortness of breath, weakness, or slurring of speech, and to report any of these symptoms to their health care provider immediately [see Warnings and Precautions (5)].

Gastrointestinal Bleeding, Ulceration, and Perforation

Advise patients to report symptoms of ulcerations and bleeding, including epigastric pain, dyspepsia, melena, and hematemesis to their health care provider. In the setting of concomitant use of low-dose aspirin for cardiac prophylaxis, inform patients of the increased risk for and the signs and symptoms of GI bleeding [see Warnings and Precautions (5)].

Hepatotoxicity

Inform patients of the warning signs and symptoms of hepatotoxicity (e.g., nausea, fatigue, lethargy, pruritus, diarrhea, jaundice, right upper quadrant tenderness, and "flu-like" symptoms). If these occur, instruct patients to stop flurbiprofen and seek immediate medical therapy [see Warnings and Precautions (5)].

Heart Failure and Edema

Advise patients to be alert for the symptoms of congestive heart failure including shortness of breath, unexplained weight gain, or edema and to contact their healthcare provider if such symptoms occur [see Warnings and Precautions (5)].

Anaphylactic Reactions

Inform patients of the signs of an anaphylactic reaction (e.g., difficulty breathing, swelling of the face or throat). Instruct patients to seek immediate emergency help if these occur [see Contraindications (4) and Warnings and Precautions (5)].

Serious Skin Reactions, including DRESS

Advise patients to stop taking flurbiprofen immediately if they develop any type of rash or fever and to contact their healthcare provider as soon as possible [see Warnings and Precautions (5.9, 5.10)].

Female Fertility

Advise females of reproductive potential who desire pregnancy that NSAIDs, including flurbiprofen, may be associated with a reversible delay in ovulation [see Use in Specific Populations (8.3)].

Fetal Toxicity

Inform pregnant women to avoid use of flurbiprofen and other NSAIDs starting at 30 weeks gestation because of the risk of the premature closing of the fetal ductus arteriosus. If treatment with flurbiprofen is needed for a pregnant woman between about 20 to 30 weeks gestation, advise her that she may need to be monitored for oligohydramnios, if treatment continues for longer than 48 hours [see Warnings and Precautions (5.11) and Use in Specific Populations (8.1)].

Avoid Concomitant Use of NSAIDs

Inform patients that the concomitant use of flurbiprofen with other NSAIDs or salicylates (e.g., diflunisal, salsalate) is not recommended due to the increased risk of gastrointestinal toxicity, and little or no increase in efficacy [see Warnings and Precautions (5) and Drug Interactions (7)]. Alert patients that NSAIDs may be present in "over the counter" medications for treatment of colds, fever, or insomnia.

Use of NSAIDS and Low-Dose Aspirin

Inform patients not to use low-dose aspirin concomitantly with flurbiprofen until they talk Dispense with Medication Guide available at: www.genuslifesciences.com/medguides to their healthcare provider [see Drug Interactions (7)].

Dispense with Medication Guide available at: www.genuslifesciences.com/medguides

Manufactured For:
Genus Lifesciences Inc.
Allentown, PA 18102

Rev. 07/2025

EM 16031/a

20769801

Medication Guide for Nonsteroidal Anti-inflammatory Drugs (NSAIDs).

What is the most important information I should know about medicines called Nonsteroidal Anti- inflammatory Drugs (NSAIDs)?
NSAIDs can cause serious side effects, including:

- Increased risk of a heart attack or stroke that can lead to death. This risk may happen early in treatment and may increase:
  - with increasing doses of NSAIDs
  - with longer use of NSAIDs

Do not take NSAIDs right before or after a heart surgery called a "coronary artery bypass graft (CABG)."
Avoid taking NSAIDs after a recent heart attack, unless your healthcare provider tells you to. You may have an increased risk of another heart attack if you take NSAIDs after a recent heart attack.

- Increased risk of bleeding, ulcers, and tears (perforation) of the esophagus (tube leading from the mouth to the stomach), stomach and intestines:
  - anytime during use
  - without warning symptoms
  - that may cause death

The risk of getting an ulcer or bleeding increases with:

- past history of stomach ulcers, or stomach or intestinal bleeding with use of NSAIDs
- taking medicines called "corticosteroids", "anticoagulants", "SSRIs" or "SNRIs"

- increasing doses of NSAIDs
- longer use of NSAIDs
- smoking
- drinking alcohol

- older age
- poor health
- advanced liver disease
- bleeding problems

NSAIDs should only be used:

- exactly as prescribed
- at the lowest dose possible for your treatment
- for the shortest time needed

What are NSAIDs?
NSAIDs are used to treat pain and redness, swelling, and heat (inflammation) from medical conditions such as different types of arthritis, menstrual cramps, and other types of short-term pain.

Who should not take NSAIDs?
Do not take NSAIDs:

- if you have had an asthma attack, hives, or other allergic reaction with aspirin or any other NSAIDs.
- right before or after heart bypass surgery.

Before taking NSAIDs, tell your healthcare provider about all of your medical conditions, including if you:

- have liver or kidney problems
- have high blood pressure
- have asthma
- are pregnant or plan to become pregnant. Taking NSAIDs at about 20 weeks of pregnancy or later may harm your unborn baby. If you need to take NSAIDs for more than 2 days when you are between 20 and 30 weeks of pregnancy, your healthcare provider may need to monitor the amount of fluid in your womb around your baby. You should not take NSAIDs after about 30 weeks of pregnancy.
- are breastfeeding or plan to breast feed.

Tell your healthcare provider about all of the medicines you take, including prescription or over-the-counter medicines, vitamins or herbal supplements. NSAIDs and some other medicines can interact with each other and cause serious side effects. Do not start taking any new medicine without talking to your healthcare provider first.

What are the possible side effects of NSAIDs? NSAIDs can cause serious side effects, including:
See "What is the most important information I should know about medicines called Nonsteroidal Anti-inflammatory Drugs (NSAIDs)?

- new or worse high blood pressure
- heart failure
- liver problems including liver failure
- kidney problems including kidney failure
- low red blood cells (anemia)
- life-threatening skin reactions
- life-threatening allergic reactions
- Other side effects of NSAIDs include: stomach pain, constipation, diarrhea, gas, heartburn, nausea, vomiting, and dizziness.

Get emergency help right away if you get any of the following symptoms:

- shortness of breath or trouble breathing
- chest pain
- weakness in one part or side of your body

- slurred speech
- swelling of the face or throat

Stop taking your NSAID and call your healthcare provider right away if you get any of the following symptoms:

- nausea
- more tired or weaker than usual
- diarrhea
- itching
- your skin or eyes look yellow
- indigestion or stomach pain
- flu-like symptoms

- vomit blood
- there is blood in your bowel movement or it is black and sticky like tar
- unusual weight gain
- skin rash or blisters with fever
- swelling of the arms, legs, hands and feet

If you take too much of your NSAID, call your healthcare provider or get medical help right away.
These are not all the possible side effects of NSAIDs. For more information, ask your healthcare provider or pharmacist about NSAIDs.
Call your doctor for medical advice about side effects. You may report side effects to FDA at 1-800-FDA-1088.

Other information about NSAIDs

- Aspirin is an NSAID but it does not increase the chance of a heart attack. Aspirin can cause bleeding in the brain, stomach, and intestines. Aspirin can also cause ulcers in the stomach and intestines.
- Some NSAIDs are sold in lower doses without a prescription (over-the-counter). Talk to your healthcare provider before using over-the-counter NSAIDs for more than 10 days.

General information about the safe and effective use of NSAIDs
Medicines are sometimes prescribed for purposes other than those listed in a Medication Guide. Do not use NSAIDs for a condition for which it was not prescribed. Do not give NSAIDs to other people, even if they have the same symptoms that you have. It may harm them.
If you would like more information about NSAIDs, talk with your healthcare provider. You can ask your pharmacist or healthcare provider for information about NSAIDs that is written for health professionals.

Manufactured For: Genus Lifesciences Inc.
Allentown, PA 18102

This Medication Guide has been approved by the U.S. Food and Drug Administration.
Rev. 07/2025

PRINCIPAL DISPLAY PANEL - 100 mg Tablet Bottle Label

NDC 64950-218-10

Flurbiprofen
Tablets, USP

100 mg

PHARMACIST: Dispense the
accompanying Medication
Guide to each patient.

Rx only

100 Tablets

Genus
Lifesciences Inc.